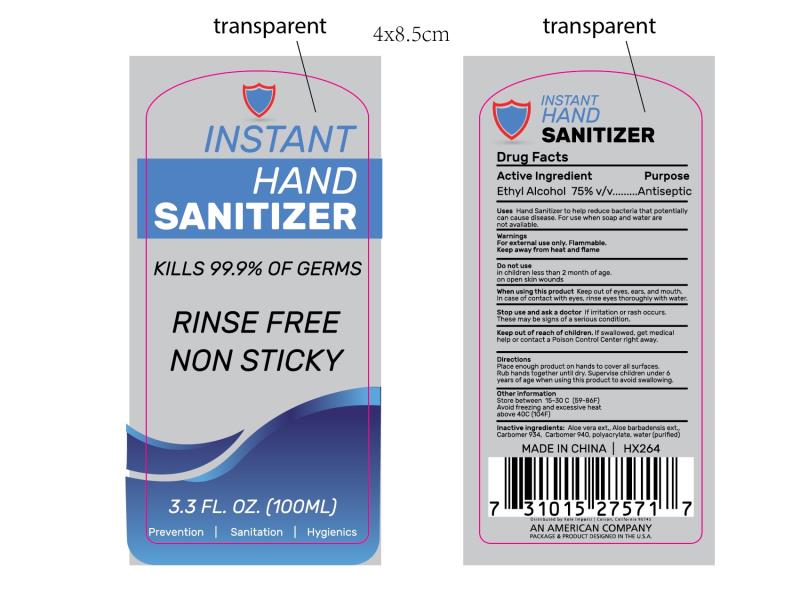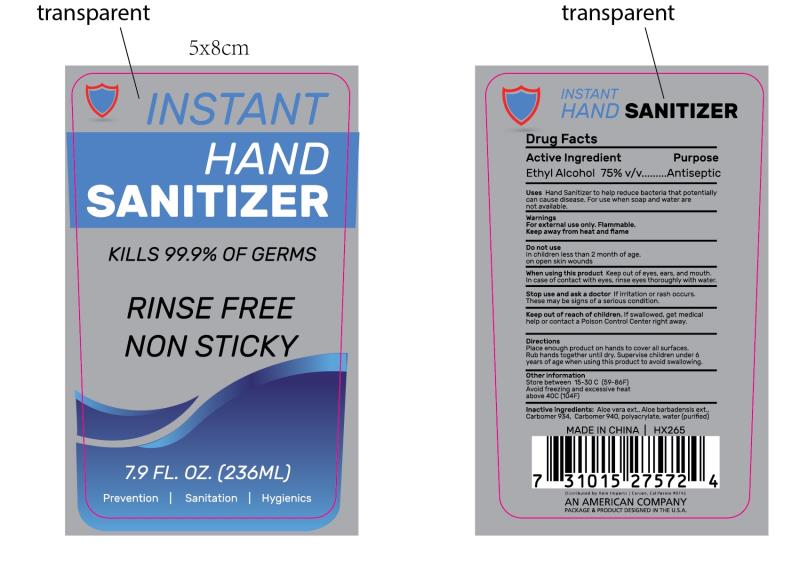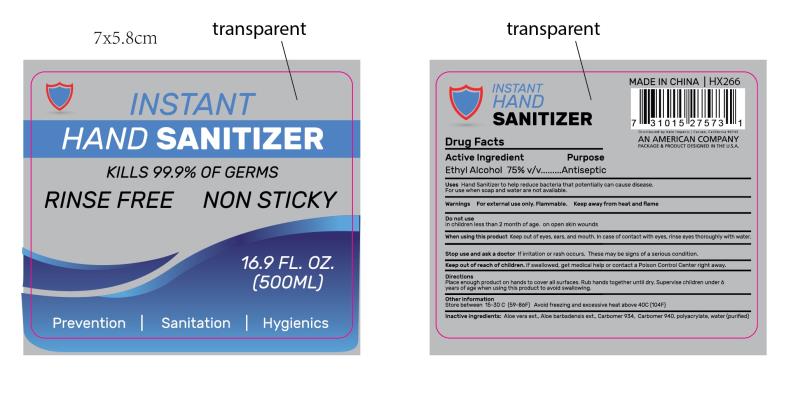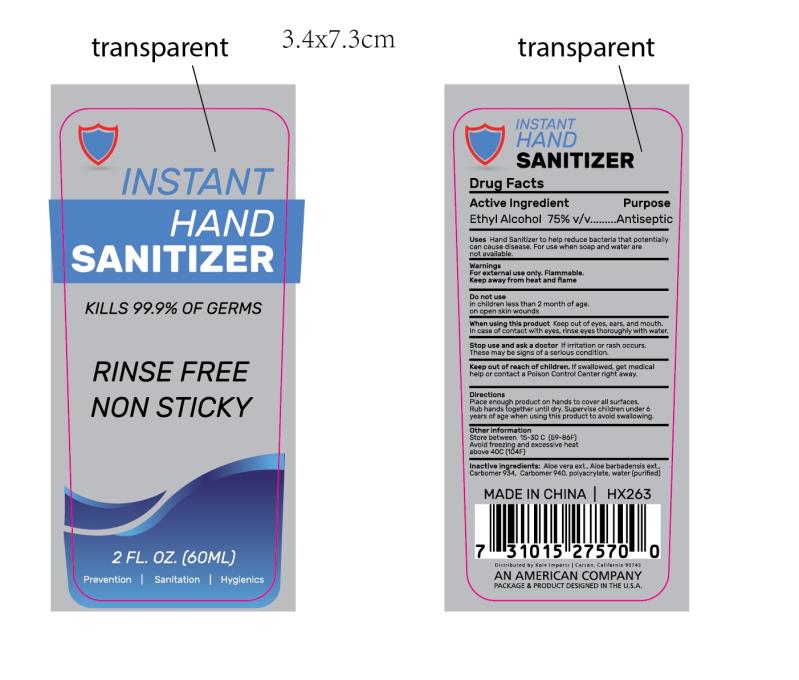 DRUG LABEL: INSTANT HAND SANITIZER
NDC: 76681-016 | Form: GEL
Manufacturer: Taizhou Huangyan Delishi Daily Necessity Co., Ltd.
Category: otc | Type: HUMAN OTC DRUG LABEL
Date: 20200515

ACTIVE INGREDIENTS: ALCOHOL 75 mL/100 mL
INACTIVE INGREDIENTS: CARBOMER 940; WATER; ALOE VERA FLOWER; ALOE VERA LEAF; CARBOMER 934

Active Ingredient(s)

Ethyl Alcohol 75% vlv. Purpose: Antiseptic

Purpose

Antiseptic

Use

Hand Sanitizer to help reduce bacteria that potentially can cause disease.

For use when soap and water are not available.

Warnings

For external use only. Flammable. Keep away from hear and flame.

Do not use

In children less than 2 month of age. On open skin wounds

WHEN USING

Keep out of eyes, ears, and mouth. In case of contact with eyes, rinse eyes thoroughly with water.

STOP USE

If irritation or rash occurs. These may be signs of a serious condition.

KEEP OUT OF REACH OF CHILDREN

If swallowed, get medical hep or contact a Poison Control Center right away.

Directions

- Place enough product on hands to cover all surfaces. Rub hands together until dry. Supervise children under 6 years of age when using this products to avoid swallowing.

Other information

- Store between 15-30 C [59-86F] Avoid freezing and excessive heat above 40C[104F]

Inactive ingredients

Aloe vera ext.

Aloe barbadensis ext.

Carbomer 934.

Carbomer 940.

polyacrylate,

water[purified]